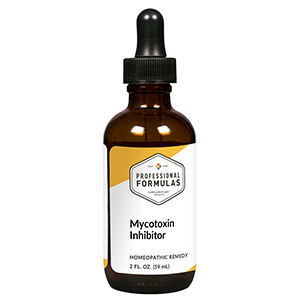 DRUG LABEL: Mycotoxin Inhibitor
NDC: 63083-6020 | Form: LIQUID
Manufacturer: Professional Complementary Health Formulas
Category: homeopathic | Type: HUMAN OTC DRUG LABEL
Date: 20190815

ACTIVE INGREDIENTS: SUS SCROFA ADRENAL GLAND 6 [hp_X]/59 mL; ARSENIC TRIOXIDE 6 [hp_X]/59 mL; COLCHICUM AUTUMNALE BULB 6 [hp_X]/59 mL; BOS TAURUS LYMPH VESSEL 6 [hp_X]/59 mL; HANDROANTHUS IMPETIGINOSUS BARK 6 [hp_X]/59 mL; BOS TAURUS SPLEEN 6 [hp_X]/59 mL; CAMPSIS RADICANS FLOWER 6 [hp_X]/59 mL; HYSSOPUS OFFICINALIS WHOLE 6 [hp_X]/59 mL; THYROID, UNSPECIFIED 6 [hp_X]/59 mL; ECHINACEA ANGUSTIFOLIA WHOLE 6 [hp_X]/59 mL; SODIUM BORATE 12 [hp_X]/59 mL; ZINC 12 [hp_X]/59 mL; LACTIC ACID, DL- 12 [hp_X]/59 mL; ASPERGILLUS FLAVUS 30 [hp_X]/59 mL; ASPERGILLUS NIGER VAR. NIGER 30 [hp_X]/59 mL; CANDIDA ALBICANS 30 [hp_X]/59 mL; CHLAMYDIA TRACHOMATIS 30 [hp_X]/59 mL; PENICILLIN G 30 [hp_X]/59 mL; YEAST, UNSPECIFIED 30 [hp_X]/59 mL
INACTIVE INGREDIENTS: ALCOHOL; WATER

X20

ACTIVE INGREDIENTS

Adrenal 6X
Arsenicum album 6X
Colchicum autumnale 6X
Lymph 6X
Pau D'Arco 6X
Spleen 6X
Tecoma radicans 6X
Thymus 6X
Thyroid 6X
Echinacea angustifolia 6X, 12X
Borax 12X
Zincum metallicum 12X
L+ Lactic acid 12X, 30X
Aspergillus flavus 30X, 60X
Aspergillus niger 30X, 60X
Candida albicans 30X, 60X
Chlamydia trachomatis 30X, 60X
Mycosis fungoides 30X, 60X
Penicillinum 30X, 60X
Saccharomyces 30X, 60X

QUESTIONS

Professional Formulas

PO Box 2034 Lake Oswego, OR 97035

INDICATIONS

For the temporary relief of cough, runny nose, itchy or watery eyes, difficulty breathing, minor joint pain, occasional headache, bloating, lack of focus, or fatigue.*

PURPOSE

*Claims based on traditional homeopathic practice, not accepted medical evidence. Not FDA evaluated.

WARNINGS

Persistent symptoms may be a sign of a serious condition. If symptoms persist or are accompanied by a fever, rash, or persistent headache, consult a doctor. Keep out of the reach of children. In case of overdose, get medical help or contact a poison control center right away. If pregnant or breastfeeding, ask a healthcare professional before use.

Keep out of the reach of children.

PREGNANCY OR BREAST FEEDING

If pregnant or breastfeeding, ask a healthcare professional before use.

DIRECTIONS

Place drops under tongue 30 minutes before/after meals. Adults and children 12 years and over: Take 10 drops up to 3 times per day. Consult a physician for use in children under 12 years of age.

OTHER INFORMATION

Tamper resistant. If seal is broken, do not use. After opening, close container tightly and store at room temperature away from heat.

INACTIVE INGREDIENTS

20% ethanol, purified water.

LABEL

Est 1985

Professional Formulas

Complementary Health

Mycotoxin Inhibitor

Homeopathic Remedy

2 FL. OZ. (59 mL)